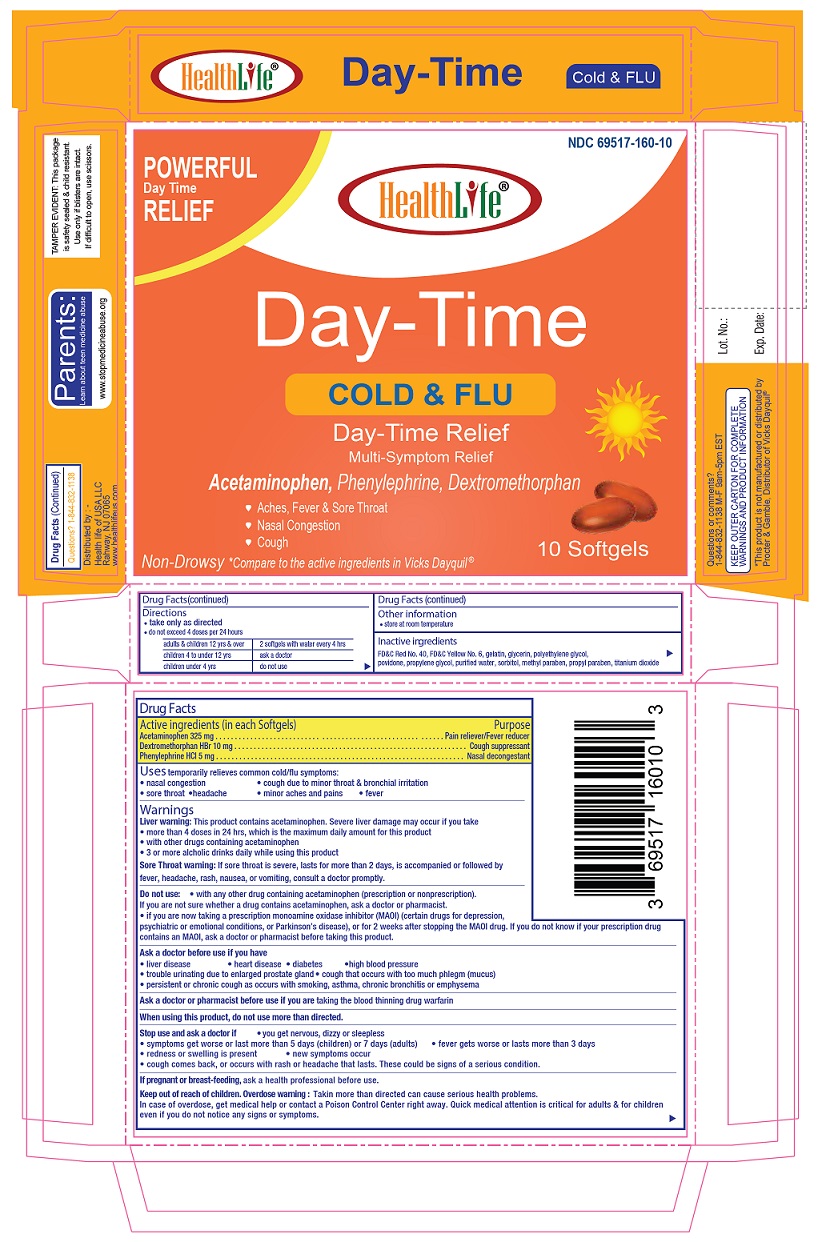 DRUG LABEL: Day-Time Cold and Flu Relief
NDC: 69517-160 | Form: CAPSULE, LIQUID FILLED
Manufacturer: HealthLife of USA
Category: otc | Type: HUMAN OTC DRUG LABEL
Date: 20231021

ACTIVE INGREDIENTS: ACETAMINOPHEN 325 mg/1 1; DEXTROMETHORPHAN HYDROBROMIDE 10 mg/1 1; PHENYLEPHRINE HYDROCHLORIDE 5 mg/1 1
INACTIVE INGREDIENTS: FD&C RED NO. 40; FD&C YELLOW NO. 6; GELATIN; GLYCERIN; POLYETHYLENE GLYCOL 400; POVIDONE K30; PROPYLENE GLYCOL; WATER; SORBITOL; METHYLPARABEN; PROPYLPARABEN; TITANIUM DIOXIDE

Day-Time Cold & Flu Relief

Active ingredients (in each Softgels)

Acetaminophen 325 mg

Dextromethorphan HBr 10 mg

Phenylephrine HCl 5 mg

Purpose

Pain reliever/Fever reducer

Cough suppressant

Nasal decongestant

Uses

temporarily relieves common cold/flu symptoms:

- nasal congestion
- cough due to minor throat & bronchial irritation
- sore throat
- headache
- minor aches and pains
- fever

Warnings

Liver warning: This product contains acetaminophen. Severe liver damage may occur if you take

- more than 4 doses in 24 hrs, which is the maximum daily amount for this product
- with other drugs containing acetaminophen
- 3 or more alcoholic drinks daily while using this product

Sore Throat warning: If sore throat is severe, lasts for more than 2 days, is accompanied or followed by fever, headache, rash, nausea, or vomiting, consult a doctor promptly.

Do not use

- with any other drug containing acetaminophen (prescription or nonprescription).
- if you are not sure whether a drug contains acetaminophen, ask a doctor or pharmacist.
- if you are now taking a prescription monoamine oxidase inhibitor (MAOI) (certain drugs for depression, psychiatric or emotional conditions, or Parkinson’s disease), or for 2 weeks after stopping the MAOI drug. If you do not know if your prescription drug contains an MAOI, ask a doctor or pharmacist before taking this product.

Ask a doctor before use if you have

- liver disease
- heart disease
- diabetes
- high blood pressure
- trouble urinating due to enlarged prostate gland
- cough that occurs with too much phlegm (mucus)
- persistent or chronic cough as occurs with smoking, asthma, chronic bronchitis or emphysema

Ask a doctor or pharmacist before use if you are taking the blood thinning drug warfarin

When using this product, do not use more than directed.

Stop use and ask a doctor if

- you get nervous, dizzy or sleepless
- symptoms get worse or last more than 5 days (children) or 7 days (adults)
- fever gets worse or lasts more than 3 days
- redness or swelling is present
- new symptoms occur
- cough comes back, or occurs with rash or headache that lasts. These could be signs of a serious condition.

If pregnant or breast-feeding, ask a health professional before use.

Keep out of reach of children. Overdose warning:

Taking more than directed can cause serious health problems. In case of overdose, get medical help or contact a Poison Control Center right away. Quick medical attention is critical for adults & for children even if you do not notice any signs or symptoms.

Direction

- take only as directed
- do not exceed 4 doses per 24 hours

adults & children 12 yrs & over | 2 softgels with water every 4 hrs
children 4 to under 12 yrs | ask a doctor
children under 4 yrs | do not use

Other information

- store at room temperature.
- TAMPER EVIDENT: This package is safety sealed & child resistant. Use only if blisters are intact. If difficult to open, use scissors.
- KEEP OUTER CARTON FOR COMPLETE WARNINGS AND PRODUCT INFORMATION

Inactive ingredients

FD&C Red No.40, FD&C Yellow No. 6, gelatin, glycerin, polyethylene glycol, povidone, propylene glycol, purified water, sorbitol, methyl paraben, propyl paraben, titanium dioxide.

Questions or comments?

1-844-832-1138

M-F 9am-5pm EST

Distributed by:

Health life of USA LLC
Rahway, NJ 07065
www.healthlifeus.com

*This product is not manufactured or distributed by Procter & Gamble, Distributor of Vicks Dayquil®

PACKAGE LABEL

NDC 69517-160-10

10 Softgels

Day-Time Cold & Flu Relief

Acetaminophen, Phenylephrine, Dextromethorphan

- Aches, Fever & Sore Throat
- Nasal Congestion
- Cough

*Compare to the active ingredients in Vicks Dayquil®